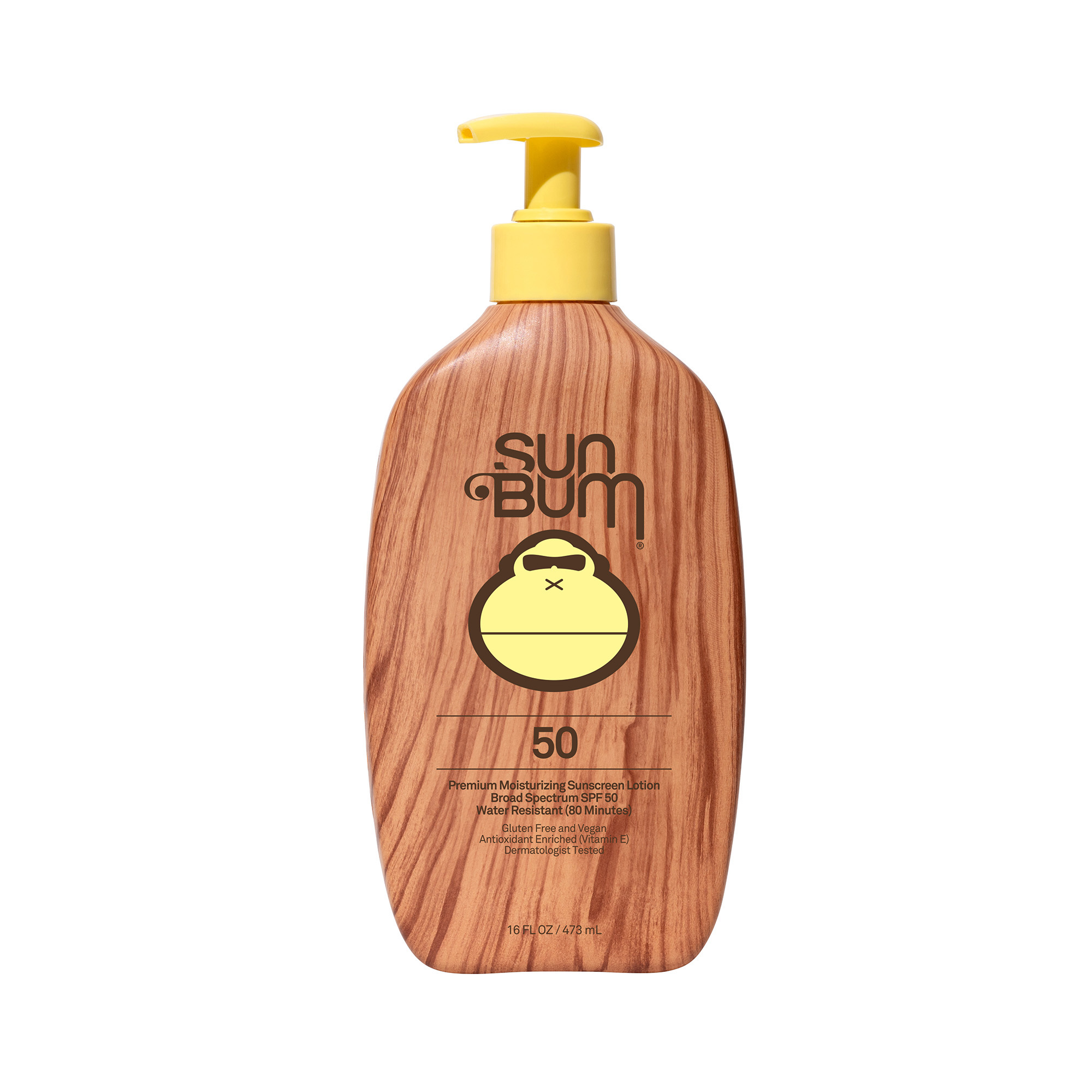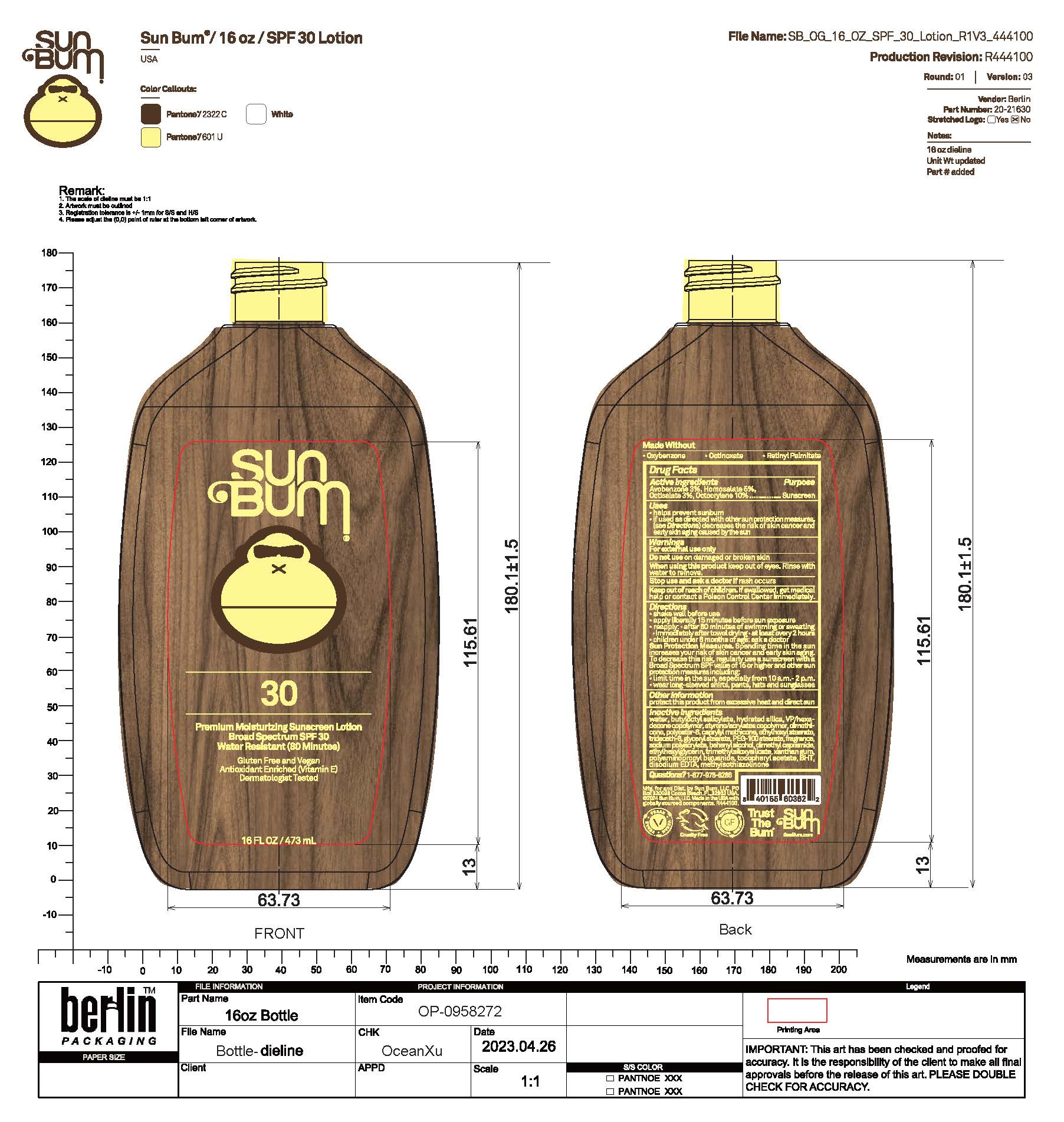 DRUG LABEL: Sun Bum 50 Premium Moisturizing Sunscreen
NDC: 69039-673 | Form: LOTION
Manufacturer: Sun Bum, LLC
Category: otc | Type: HUMAN OTC DRUG LABEL
Date: 20250821

ACTIVE INGREDIENTS: OCTISALATE 50 mg/1 mL; AVOBENZONE 30 mg/1 mL; HOMOSALATE 100 mg/1 mL; OCTOCRYLENE 100 mg/1 mL
INACTIVE INGREDIENTS: EDETATE DISODIUM; BEHENYL ALCOHOL; BHT; METHYLISOTHIAZOLINONE; .ALPHA.-TOCOPHEROL ACETATE; TRIDECETH-6; GLYCERYL STEARATE; POLYAMINOPROPYL BIGUANIDE; ETHYLHEXYL STEARATE; ETHYLHEXYLGLYCERIN; XANTHAN GUM; TRIMETHYLSILOXYSILICATE (M/Q 0.6-0.8); BUTYLOCTYL SALICYLATE; CAPRYLYL METHICONE; PEG-100 STEARATE; SODIUM POLYACRYLATE (2500000 MW); DIMETHYL CAPRAMIDE; POLYESTER-8 (1400 MW, CYANODIPHENYLPROPENOYL CAPPED); STYRENE/AMMONIUM ACRYLATE COPOLYMER (300000 MW); HYDRATED SILICA; DIMETHICONE; VP/HEXADECENE COPOLYMER; WATER

Sun Bum 50 Premium Moisturizing Sunscreen

Purpose

Sunscreen

Active ingredients

Avobenzone 3%, Homosalate 10%, Octisalate 5%, Octocrylene 10%

Uses

• helps prevent sunburn • if used as directed with other sun protection measures, (see Directions) decreases the risk of skin cancer and early skin aging caused by the sun

Warnings

For external use only

Do not use on damaged or broken skin

When using this product keep out of eyes. Rinse with water to remove.

Stop use and ask a doctor if rash occurs

Keep out of reach of children. If swallowed, get medical help or contact a Poison Control Center immediately.

Warnings

Keep Out Of Reach Of Children

Directions

• shake well before use

• apply liberally 15 minutes before sun exposure

• reapply: • after 80 minutes of swimming or sweating • immediately after towel drying • at least every 2 hours

• children under 6 months of age: ask a doctor

• Sun Protection Measures. Spending time in the sun increases your risk of skin cancer and early skin aging. To decrease this risk, regularly use a sunscreen with a Broad Spectrum SPF value of 15 or higher and other sun protection measures including:

• limit time in the sun, especially from 10 a.m.- 2 p.m.

• wear long-sleeved shirts, pants, hats and sunglasses

Directions

• shake well before use

• apply liberally 15 minutes before sun exposure

Other information

protect this product from excessive heat and direct sun

Inactive ingredients

water, butyloctyl salicylate, hydrated silica, VP/hexadecene copolymer, styrene/acrylates copolymer, dimethicone, polyester-8, caprylyl methicone, ethylhexyl stearate, trideceth-6, glyceryl stearate, PEG-100 stearate, fragrance, sodium polyacrylate, behenyl alcohol, dimethyl capramide, ethylhexylglycerin, trimethylsiloxysilicate, xanthan gum, polyaminopropyl biguanide, tocopheryl acetate, BHT, disodium EDTA, methylisothiazolinone

Questions

Questions? 1-877-978-6286